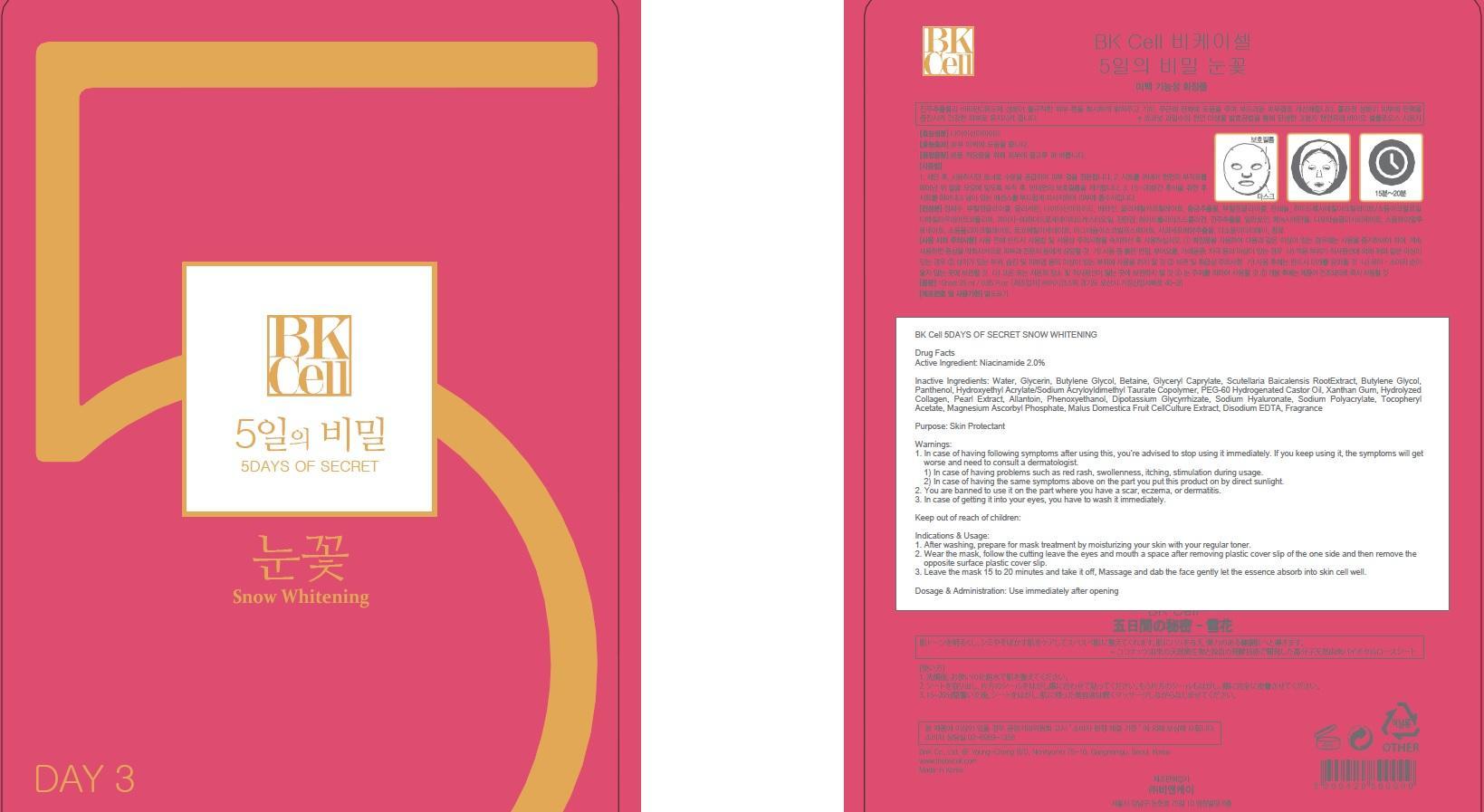 DRUG LABEL: BK Cell 5DAYS OF SECRET SNOW WHITENING
NDC: 69946-030 | Form: PATCH
Manufacturer: BNK CO., LTD.
Category: otc | Type: HUMAN OTC DRUG LABEL
Date: 20150715

ACTIVE INGREDIENTS: Niacinamide 0.5 mg/25 mL
INACTIVE INGREDIENTS: Water; Glycerin

ACTIVE INGREDIENT

Active Ingredient: Niacinamide 2.0%

INACTIVE INGREDIENT

Inactive Ingredients: Water, Glycerin, Butylene Glycol, Betaine, Glyceryl Caprylate, Scutellaria Baicalensis RootExtract, Butylene Glycol, Panthenol, Hydroxyethyl Acrylate/Sodium Acryloyldimethyl Taurate Copolymer, PEG-60 Hydrogenated Castor Oil, Xanthan Gum, Hydrolyzed Collagen, Pearl Extract, Allantoin, Phenoxyethanol, Dipotassium Glycyrrhizate, Sodium Hyaluronate, Sodium Polyacrylate, Tocopheryl Acetate, Magnesium Ascorbyl Phosphate, Malus Domestica Fruit CellCulture Extract, Disodium EDTA, Fragrance

PURPOSE

Purpose: Skin Protectant

WARNINGS

Warnings: 1. In case of having following symptoms after using this, you're advised to stop using it immediately. If you keep using it, the symptoms will get worse and need to consult a dermatologist. 1) In case of having problems such as red rash, swollenness, itching, stimulation during usage. 2) In case of having the same symptoms above on the part you put this product on by direct sunlight. 2. You are banned to use it on the part where you have a scar, eczema, or dermatitis. 3. In case of getting it into your eyes, you have to wash it immediately.

KEEP OUT OF REACH OF CHILDREN

Keep out of reach of babies and children

INDICATIONS & USAGE

Indications & Usage: 1. After washing, prepare for mask treatment by moisturizing your skin with your regular toner. 2. Wear the mask, follow the cutting leave the eyes and mouth a space after removing plastic cover slip of the one side and then remove the opposite surface plastic cover slip. 3. Leave the mask 15 to 20 minutes and take it off, Massage and dab the face gently let the essence absorb into skin cell well.

DOSAGE & ADMINISTRATION

Dosage & Administration: Use immediately after opening